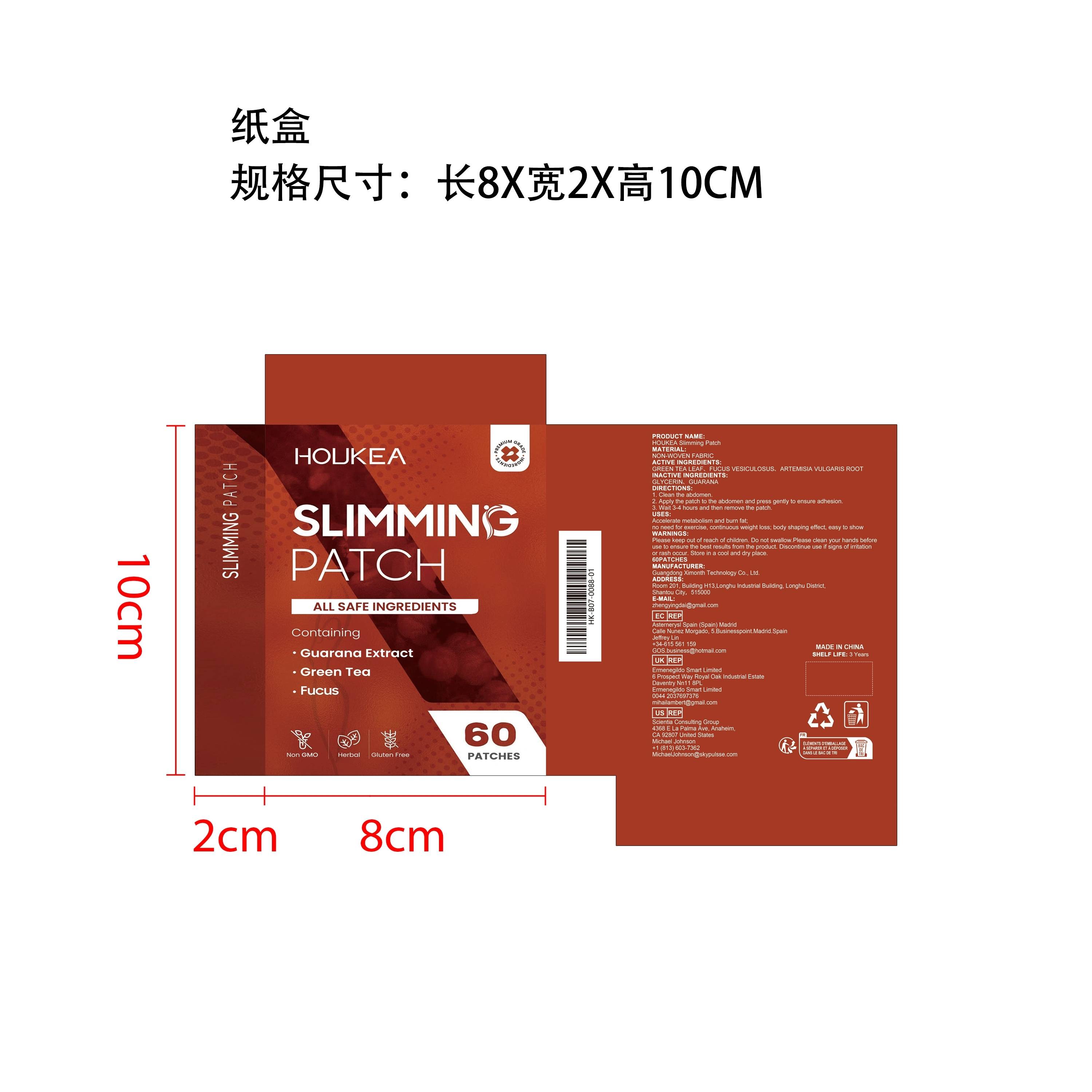 DRUG LABEL: HOUKEA Slimming Patch
NDC: 84660-098 | Form: PATCH
Manufacturer: Guangdong Ximonth Technology Co., Ltd.
Category: otc | Type: HUMAN OTC DRUG LABEL
Date: 20241031

ACTIVE INGREDIENTS: FUCUS VESICULOSUS 10 g/60 g; ARTEMISIA VULGARIS ROOT 10 g/60 g; GREEN TEA LEAF 10 g/60 g
INACTIVE INGREDIENTS: GUARANA 10 g/60 g; GLYCERIN 20 g/60 g

Active Ingredient(s)

GREEN TEA LEAF、FUCUS VESICULOSUS、ARTEMISIA VULGARIS ROOT

Purpose

Accelerate metabolism and burn fat；no need for exercise, continuous weight loss; body shaping effect, easy to show

Use

1. Clean the abdomen.
2. Apply the patch to the abdomen and press gently to ensure adhesion.
3. Wait 3-4 hours and then remove the patch.

Warnings

Please keep out of reach of children.Do not swallow.Please clean your hands before use to ensure the best results from the product.Discontinue use if signs of irritation or rash occur.Store in a cool and dry place.

Do not use

Discontinue use if signs of irritation or rash occur.

Stop Use

Discontinue use if signs of irritation or rash occur

KEEP OUT OF REACH OF CHILDREN

Please keep out of reach of children. Do not swallow.

STORAGE AND HANDLING

Store in a cool and dry place.

INACTIVE INGREDIENT

GLYCERIN、GUARANA